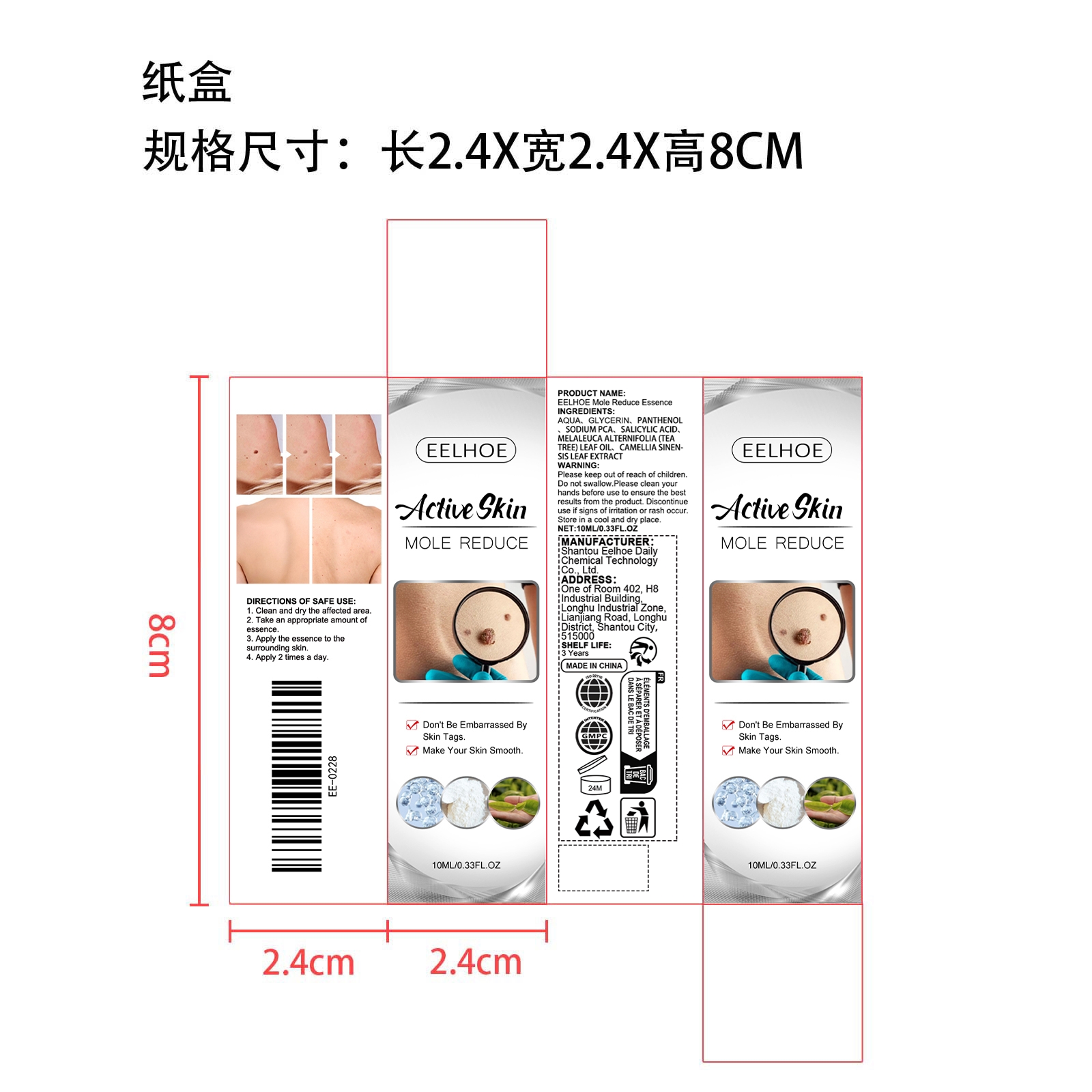 DRUG LABEL: EELHOE Mole Reduce Essence
NDC: 85064-002 | Form: LIQUID
Manufacturer: Shantou Eelhoe Daily Chemical Technology Co., Ltd.
Category: otc | Type: HUMAN OTC DRUG LABEL
Date: 20251127

ACTIVE INGREDIENTS: CAMELLIA SINENSIS LEAF 0.002 mg/10 mg; MELALEUCA ALTERNIFOLIA (TEA TREE) LEAF OIL 0.002 mg/10 mg
INACTIVE INGREDIENTS: GLYCERIN 0.4 mg/10 mg; AQUA 9.344 mg/10 mg; PANTHENOL 0.15 mg/10 mg; SODIUM PCA 0.1 mg/10 mg; SALICYLIC ACID 0.002 mg/10 mg

INACTIVE INGREDIENT

AQUA, GLYCERIN, PANTHENOL 、SODIUM PCA、 SALICYLIC ACID

ACTIVE INGREDIENT

MELALEUCA ALTERNIFOLIA (TEA TREE）LEAF OIL、CAMELLIA SINENSIS LEAF

PURPOSE

Don't Be Embarrassed By Skin Tags.
Make Your Skin Smooth.

WHEN USING

1.Clean and dry the affected area.

2. Take an appropriate amount of essence.

3. Apply the essence to the surrounding skin.

4. Apply 2 times a day.

WARNINGS

Please keep out of reach of children.Do not swallow.Please clean your hands before use to ensure the best results from the product.Discontinue use if signs of irritation or rash occur. Store in a cool and dry place.

KEEP OUT OF REACH OF CHILDREN

Please keep out of reach of children.Do not swallow.

STOP USE

Discontinue use if signs of irritation or rash occur.

DO NOT USE

Discontinue use if signs of irritation or rash occur.

STORAGE AND HANDLING

Store in a cool and dry place.